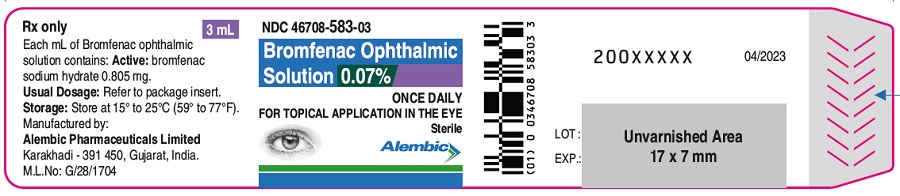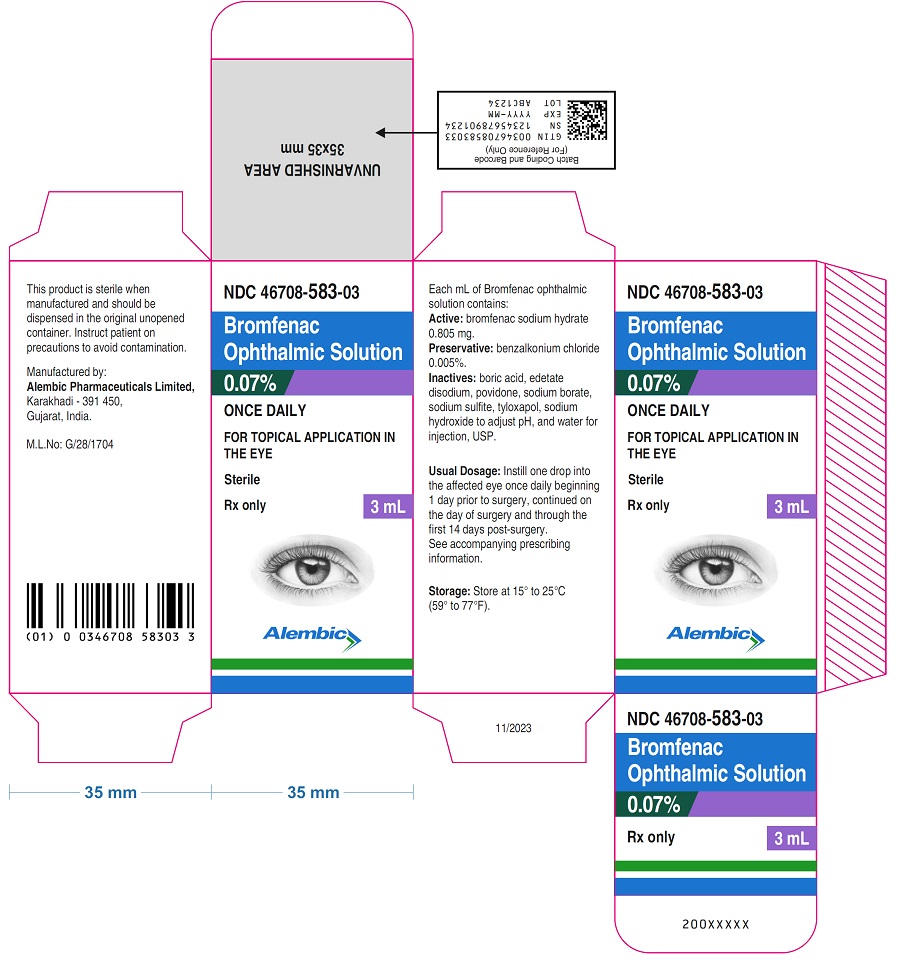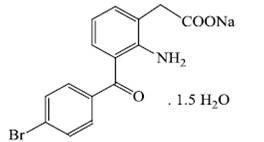 DRUG LABEL: BROMFENAC SODIUM
NDC: 46708-583 | Form: SOLUTION/ DROPS
Manufacturer: Alembic Pharmaceuticals Limited
Category: prescription | Type: Human Prescription Drug Label
Date: 20240709

ACTIVE INGREDIENTS: BROMFENAC SODIUM 0.805 mg/1 mL
INACTIVE INGREDIENTS: BENZALKONIUM CHLORIDE; BORIC ACID; EDETATE DISODIUM; POVIDONE; SODIUM BORATE; SODIUM SULFITE; TYLOXAPOL; SODIUM HYDROXIDE; WATER

HIGHLIGHTS OF PRESCRIBING INFORMATION

These highlights do not include all the information needed to use BROMFENAC OPHTHALMIC SOLUTION 0.07% safely and effectively. See full prescribing information for BROMFENAC OPHTHALMIC SOLUTION.
BROMFENAC Ophthalmic Solution 0.07%
Initial U.S. Approval: 1997

1 INDICATIONS AND USAGE

BROMFENAC is a nonsteroidal anti-inflammatory drug (NSAID) indicated for the treatment of postoperative inflammation and reduction of ocular pain in patients who have undergone cataract surgery. (1).

2 DOSAGE AND ADMINISTRATION

Instill one drop into the affected eye once daily beginning 1 day prior to surgery, continued on the day of surgery, and through the first 14 days post-surgery. (2.1).

3 DOSAGE FORMS AND STRENGTHS

Topical ophthalmic solution: bromfenac 0.07%

4 CONTRAINDICATIONS

None

5 WARNINGS AND PRECAUTIONS

- Sulfite Allergic Reactions (5.1)
- Slow or Delayed Healing (5.2)
- Potential for cross-sensitivity (5.3)
- Increase bleeding of ocular tissues (5.4)
- Corneal effects including keratitis (5.5)
- Contact Lens Wear (5.6)

6 ADVERSE REACTIONS

The most commonly reported adverse reactions in 3 to 8% of patients were anterior chamber inflammation, foreign body sensation, eye pain, photophobia, and vision blurred. (6.1).
To report SUSPECTED ADVERSE REACTIONS, contact Alembic Pharmaceuticals, Inc. at 1-866-210-9797 or FDA at 1-800-FDA-1088 or www.fda.gov/medwatch.

FULL PRESCRIBING INFORMATION

1 INDICATIONS AND USAGE

Bromfenac ophthalmic solution 0.07% is indicated for the treatment of postoperative inflammation and reduction of ocular pain in patients who have undergone cataract surgery.

2 DOSAGE AND ADMINISTRATION

2.1 Recommended Dosing

One drop of Bromfenac ophthalmic solution should be applied to the affected eye once daily beginning 1 day prior to cataract surgery, continued on the day of surgery, and through the first 14 days of the postoperative period.

2.2 Use with Other Topical Ophthalmic Medications

Bromfenac ophthalmic solution may be administered in conjunction with other topical ophthalmic medications such as alpha-agonists, beta-blockers, carbonic anhydrase inhibitors, cycloplegics, and mydriatics. Drops should be administered at least 5 minutes apart.

3 DOSAGE FORMS AND STRENGTHS

Topical ophthalmic solution: bromfenac 0.07%.

4 CONTRAINDICATIONS

None.

5 WARNINGS AND PRECAUTIONS

5.1 Sulfite Allergic Reactions

Bromfenac ophthalmic solution contains sodium sulfite, a sulfite that may cause allergic type reactions including anaphylactic symptoms and life-threatening or less severe asthmatic episodes in certain susceptible people. The overall prevalence of sulfite sensitivity in the general population is unknown and probably low. Sulfite sensitivity is seen more frequently in asthmatic than in non-asthmatic people.

5.2 Slow or Delayed Healing

All topical nonsteroidal anti-inflammatory drugs (NSAIDs), including bromfenac, may slow or delay healing. Topical corticosteroids are also known to slow or delay healing. Concomitant use of topical NSAIDs and topical steroids may increase the potential for healing problems.

5.3 Potential for Cross-Sensitivity

There is the potential for cross-sensitivity to acetylsalicylic acid, phenylacetic acid derivatives, and other NSAIDs, including bromfenac. Therefore, caution should be used when treating individuals who have previously exhibited sensitivities to these drugs.

5.4 Increased Bleeding Time

With some NSAIDs, including bromfenac, there exists the potential for increased bleeding time due to interference with platelet aggregation. There have been reports that ocularly applied NSAIDs may cause increased bleeding of ocular tissues (including hyphemas) in conjunction with ocular surgery.

It is recommended that bromfenac ophthalmic solution be used with caution in patients with known bleeding tendencies or who are receiving other medications which may prolong bleeding time.

5.5 Keratitis and Corneal Reactions

Use of topical NSAIDs may result in keratitis. In some susceptible patients, continued use of topical NSAIDs may result in epithelial breakdown, corneal thinning, corneal erosion, corneal ulceration or corneal perforation. These events may be sight threatening. Patients with evidence of corneal epithelial breakdown should immediately discontinue use of topical NSAIDs, including bromfenac, and should be closely monitored for corneal health.

Post-marketing experience with topical NSAIDs suggests that patients with complicated ocular surgeries, corneal denervation, corneal epithelial defects, diabetes mellitus, ocular surface diseases (e.g., dry eye syndrome), rheumatoid arthritis, or repeat ocular surgeries within a short period of time may be at increased risk for corneal adverse events which may become sight threatening. Topical NSAIDs should be used with caution in these patients.

Post-marketing experience with topical NSAIDs also suggests that use more than 24 hours prior to surgery or use beyond 14 days post-surgery may increase patient risk for the occurrence and severity of corneal adverse events.

5.6 Contact Lens Wear

Bromfenac ophthalmic solution should not be instilled while wearing contact lenses. Remove contact lenses prior to instillation of bromfenac ophthalmic solution. The preservative in bromfenac ophthalmic solution, benzalkonium chloride may be absorbed by soft contact lenses. Lenses may be reinserted after 10 minutes following administration of bromfenac ophthalmic solution.

6 ADVERSE REACTIONS

6.1 Clinical Trial Experience

Because clinical trials are conducted under widely varying conditions, adverse reaction rates observed in the clinical trials of a drug cannot be directly compared to rates in the clinical trials of another drug and may not reflect the rates observed in clinical practice.

The most commonly reported adverse reactions following use of bromfenac ophthalmic solution following cataract surgery include: anterior chamber inflammation, foreign body sensation, eye pain, photophobia, and vision blurred. These reactions were reported in 3 to 8% of patients.

8 USE IN SPECIFIC POPULATIONS

8.1 Pregnancy

Treatment of rats at oral doses up to 0.9 mg/kg/day (systemic exposure 90 times the systemic exposure predicted from the recommended human ophthalmic dose [RHOD] assuming the human systemic concentration is at the limit of quantification) and rabbits at oral doses up to 7.5 mg/kg/day (150 times the predicted human systemic exposure) produced no treatment-related malformations in reproduction studies. However, embryo-fetal lethality and maternal toxicity were produced in rats and rabbits at 0.9 mg/kg/day and 7.5 mg/kg/day, respectively. In rats, bromfenac treatment caused delayed parturition at 0.3 mg/kg/day (30 times the predicted human exposure) and caused dystocia, increased neonatal mortality, and reduced postnatal growth at 0.9 mg/kg/day.

There are no adequate and well-controlled studies in pregnant women. Because animal reproduction studies are not always predictive of human response, this drug should be used during pregnancy only if the potential benefit justifies the potential risk to the fetus.

Because of the known effects of prostaglandin biosynthesis-inhibiting drugs on the fetal cardiovascular system (closure of ductus arteriosus), the use of Bromfenac ophthalmic solution during late pregnancy should be avoided.

8.3 Nursing Mothers

Caution should be exercised when bromfenac ophthalmic solution is administered to a nursing woman.

8.4 Pediatric Use

Safety and efficacy in pediatric patients below the age of 18 years have not been established.

8.5 Geriatric Use

There is no evidence that the efficacy or safety profiles for bromfenac ophthalmic solution differ in patients 70 years of age and older compared to younger adult patients.

11 DESCRIPTION

Bromfenac ophthalmic solution 0.07% is a sterile, topical, nonsteroidal anti-inflammatory drug (NSAID) for ophthalmic use. Each mL of bromfenac ophthalmic solution contains 0.805 mg bromfenac sodium sesquihydrate (equivalent to 0.7 mg bromfenac free acid). The USAN name for bromfenac sodium sesquihydrate is bromfenac sodium. Bromfenac sodium is designated chemically as sodium-2-amino-3(4-bromobenzoyl)-phenylacetate sesquihydrate, with an empirical formula of C15H11BrNNaO3 . 1.5 H2O. The chemical structure for bromfenac sodium sesquihydrate is:

Bromfenac sodium is a bright orange to yellow powder. The molecular weight of bromfenac sodium is 383.17.
Bromfenac ophthalmic solution is supplied as a sterile aqueous 0.07% solution, with a pH of 7.8. The osmolality of Bromfenac ophthalmic solution is approximately 300 mOsmol/kg.
Each mL of bromfenac ophthalmic solution contains:
Active: Each mL contains bromfenac sodium sesquihydrate 0.0805%, which is equivalent to bromfenac free acid 0.07%.
Preservative: benzalkonium chloride 0.005%
Inactives: boric acid, edetate disodium, povidone, sodium borate, sodium sulfite, tyloxapol, sodium hydroxide to adjust pH and water for injection, USP.

12 CLINICAL PHARMACOLOGY

12.1 Mechanism of Action

Bromfenac is a nonsteroidal anti-inflammatory drug (NSAID) that has anti-inflammatory activity. The mechanism of its action is thought to be due to its ability to block prostaglandin synthesis by inhibiting cyclooxygenase (COX) 1 and 2. Prostaglandins have been shown in many animal models to be mediators of certain kinds of intraocular inflammation. In studies performed in animal eyes, prostaglandins have been shown to produce disruption of the blood-aqueous humor barrier, vasodilation, increased vascular permeability, leukocytosis, and increased intraocular pressure.

12.3 Pharmacokinetics

The plasma concentration of bromfenac following ocular administration of 0.07% bromfenac ophthalmic solution in humans is unknown. Based on the maximum proposed dose of one drop to each eye (0.035 mg) and PK information from other routes of administration, the systemic concentration of bromfenac is estimated to be below the limit of quantification (50 ng/mL) at steady-state in humans.

13 NONCLINICAL TOXICOLOGY

13.1 Carcinogenesis, Mutagenesis, Impairment of Fertility

Long-term carcinogenicity studies in rats and mice given oral doses of bromfenac up to 0.6 mg/kg/day (systemic exposure 30 times the systemic exposure predicted from the recommended human ophthalmic dose [RHOD] assuming the human systemic concentration is at the limit of quantification) and 5 mg/kg/day (340 times the predicted human systemic exposure), respectively, revealed no significant increases in tumor incidence.
Bromfenac did not show mutagenic potential in various mutagenicity studies, including the reverse mutation, chromosomal aberration, and micronucleus tests.

Bromfenac did not impair fertility when administered orally to male and female rats at doses up to 0.9 mg/kg/day and 0.3 mg/kg/day, respectively (systemic exposure 90 and 30 times the predicted human exposure, respectively).

14 CLINICAL STUDIES

14.1 Ocular Inflammation and Pain

Bromfenac 0.07% QD for the treatment of postoperative inflammation and reduction of ocular pain was evaluated in two multi-center, randomized, double-masked, parallel-group and placebo (vehicle)-controlled studies. Patients undergoing cataract surgery self-administered bromfenac 0.07% or vehicle once daily, beginning 1 day prior to surgery, continuing on the morning of surgery and for 14 days after surgery. Complete clearance of ocular inflammation (0 cell and no flare) was assessed on Days 1, 3, 8 and 15 post-surgery using slit lamp biomicroscopy. The pain score was self-reported. The primary efficacy endpoint was the proportion of subjects who had complete clearance of ocular inflammation by day 15. In the intent-to-treat analyses from both assessments, complete clearance at Day 8 and Day 15, bromfenac 0.07% was superior to vehicle as shown in the following table.

Proportion of Subjects with Cleared Ocular Inflammation (0 cells and no flare)
Study | Visit | Bromfenac 0.07% | Vehicle | Difference (%) (Asymptotic 95% CI)
Study 1 | At Day 8 | 27/112 (24.1%) | 7/108 (6.5%) | 17.6 (8.4, 26.8)
Study 1 | At Day 15 | 51/112 (45.5%) | 14/108 (13.0%) | 32.5 (21.4, 43.8)
Study 2 | At Day 8 | 33/110 (30.0%) | 14/110 (12.7%) | 17.3 (6.7, 27.9)
Study 2 | At Day 15 | 50/110 (45.5%) | 30/110 (27.3%) | 18.2 (5.7, 30.7)
Proportion of Subjects who Were Pain Free
Study | Visit | Bromfenac 0.07% | Vehicle | Difference (%) (Asymptotic 95% CI)
Study 1 | At Day 1 | 91/112 (81.3%) | 47/108 (43.5%) | 37.7 (25.9, 49.6)
Study 2 | At Day 1 | 84/110 (76.4%) | 61/110 (55.5%) | 20.9 (8.7, 33.1)

16 HOW SUPPLIED/STORAGE AND HANDLING

Bromfenac ophthalmic solution 0.07% is supplied in a white Opaque LDPE bottle with White Opaque LDPE nozzle and gray HDPE cap as follows:
• 3 mL in a 5 mL container (NDC 46708-583-03)
STORAGE:
Store at 15º to 25ºC (59º to 77ºF)

17 PATIENT COUNSELING INFORMATION

17.1 Slowed or Delayed Healing

Advise patients of the possibility that slow or delayed healing may occur while using NSAIDs.

17.2 Sterility of Dropper Tip

Advise patients to replace bottle cap after using and to not touch dropper tip to any surface, as this may contaminate the contents. Advise patients that a single bottle of bromfenac ophthalmic solution 0.07% be used to treat only one eye.

17.3 Concomitant Use of Contact Lenses

Advise patients to remove contact lenses prior to instillation of bromfenac ophthalmic solution 0.07%. The preservative in bromfenac ophthalmic solution 0.07%, benzalkonium chloride, may be absorbed by soft contact lenses. Lenses may be reinserted after 10 minutes following administration of bromfenac ophthalmic solution 0.07%.

17.4 Concomitant Topical Ocular Therapy

If more than one topical ophthalmic medication is being used, the medicines should be administered at least 5 minutes apart.

Rx Only

Manufactured by:
Alembic Pharmaceuticals Limited,
Karakhadi-391 450, Gujarat, India

Issued: 11/2023

PACKAGE LABEL.PRINCIPAL DISPLAY PANEL

Bromfenac ophthalmic solution, 0.07% - Bottle label - Alembic Pharmaceuticals Limited
Bromfenac ophthalmic solution, 0.07% - Carton label - Alembic Pharmaceuticals Limited